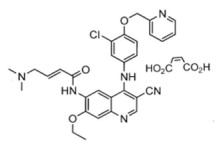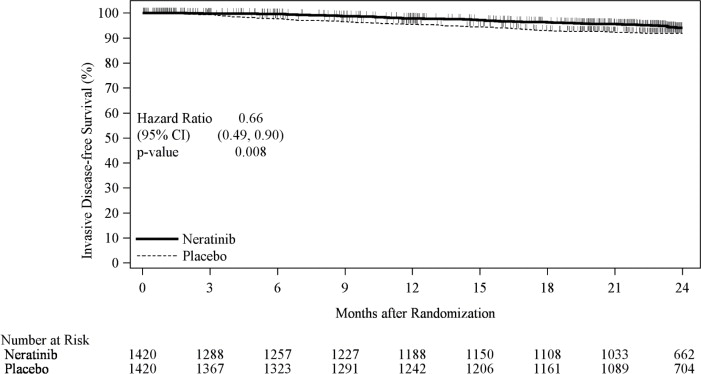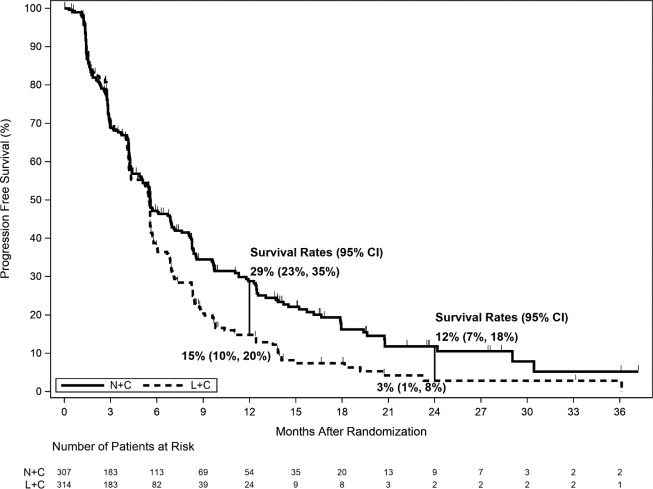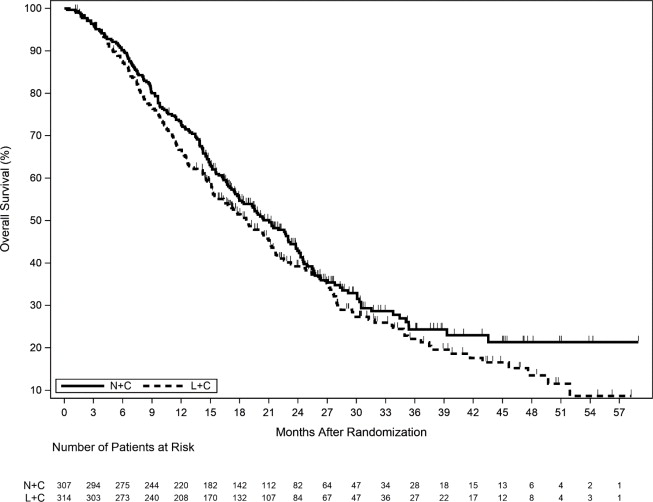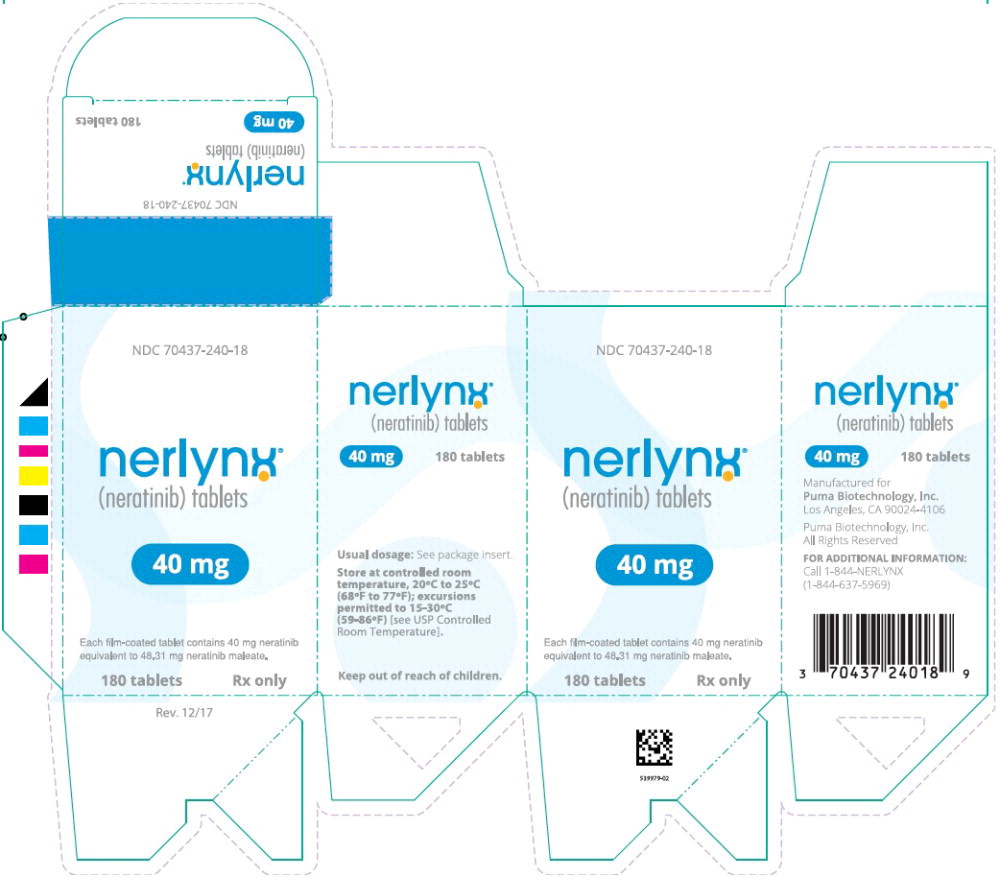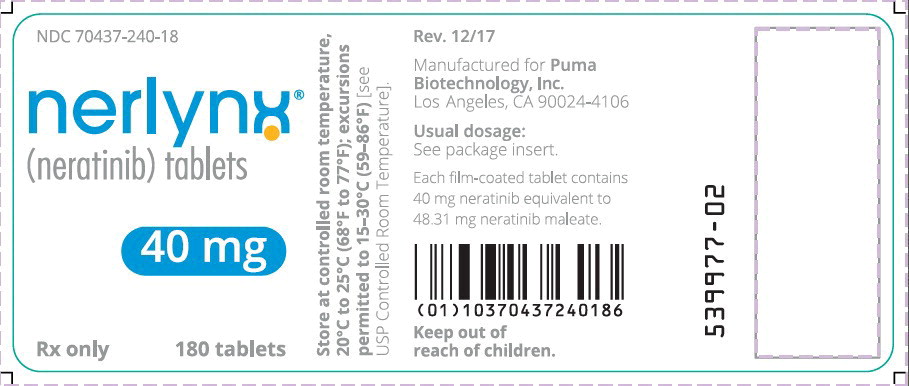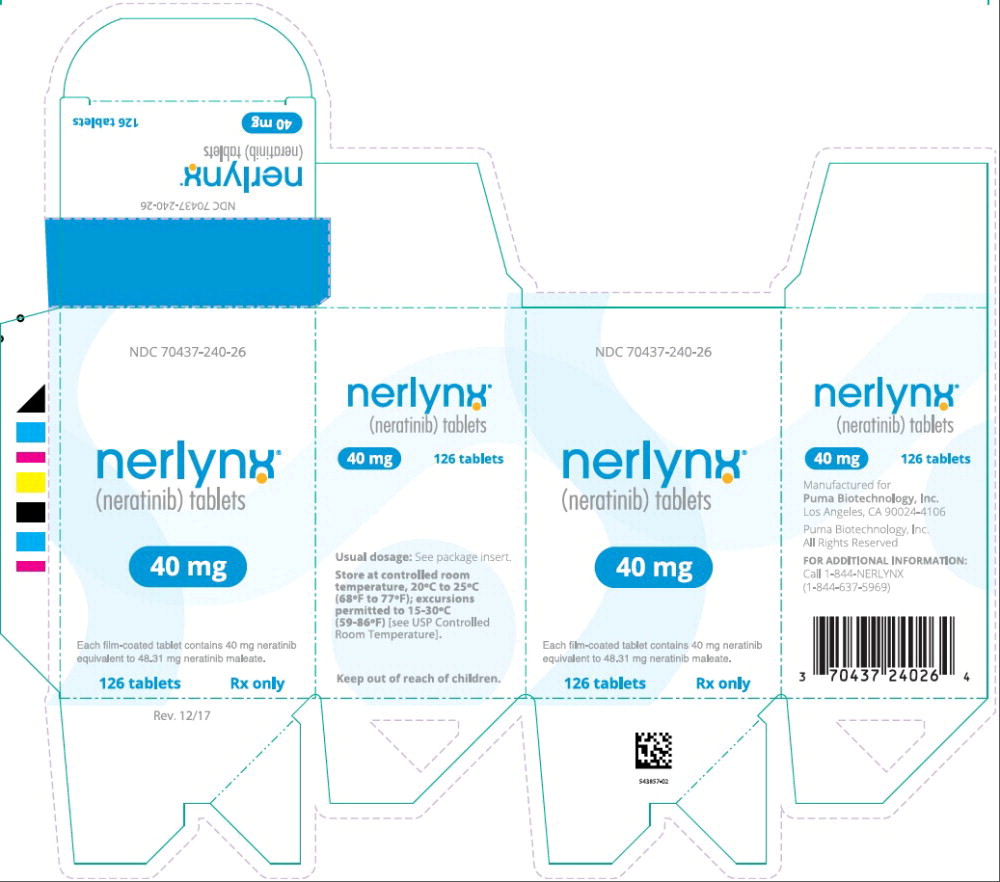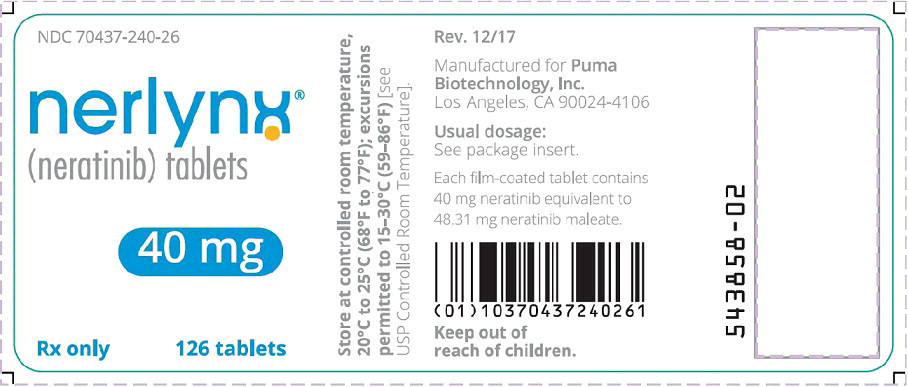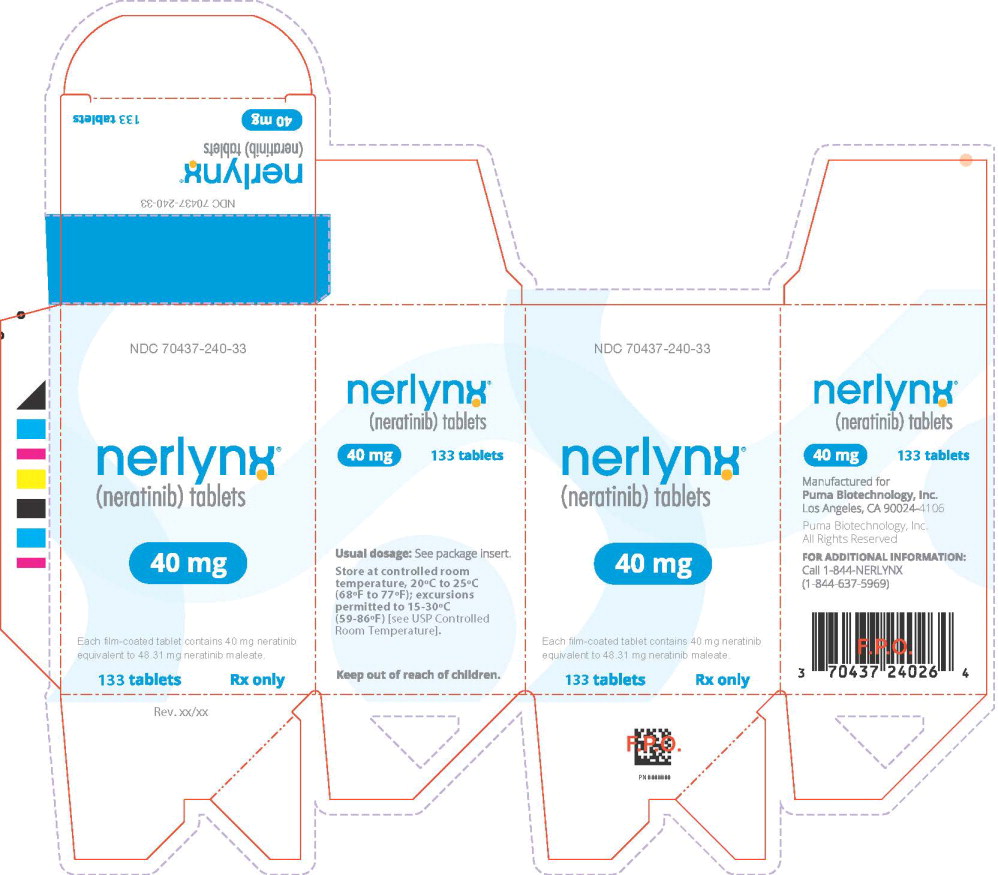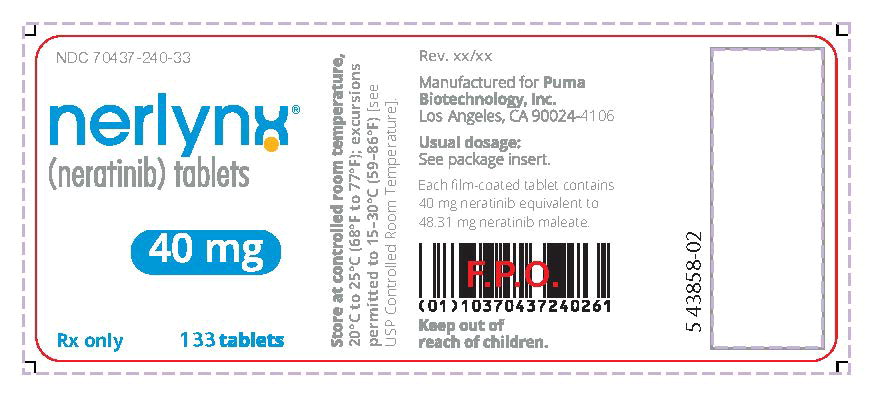 DRUG LABEL: Nerlynx
NDC: 70437-240 | Form: TABLET
Manufacturer: Puma Biotechnology, Inc.
Category: prescription | Type: HUMAN PRESCRIPTION DRUG LABEL
Date: 20251201

ACTIVE INGREDIENTS: NERATINIB MALEATE ANHYDROUS 40 mg/1 1
INACTIVE INGREDIENTS: SILICON DIOXIDE; MANNITOL; MICROCRYSTALLINE CELLULOSE; CROSPOVIDONE, UNSPECIFIED; POVIDONE, UNSPECIFIED; MAGNESIUM STEARATE; WATER; POLYVINYL ALCOHOL, UNSPECIFIED; TITANIUM DIOXIDE; POLYETHYLENE GLYCOL, UNSPECIFIED; TALC; FERRIC OXIDE RED

HIGHLIGHTS OF PRESCRIBING INFORMATION

These highlights do not include all the information needed to use NERLYNX safely and effectively. See full prescribing information for NERLYNX.
NERLYNX®(neratinib) tablets, for oral use
Initial U.S. Approval: 2017

1 INDICATIONS AND USAGE

NERLYNX is a kinase inhibitor indicated:

- As a single agent, for the extended adjuvant treatment of adult patients with early-stage HER2-positive breast cancer, to follow adjuvant trastuzumab-based therapy. (1.1)
- In combination with capecitabine, for the treatment of adult patients with advanced or metastatic HER2-positive breast cancer who have received two or more prior anti-HER2 based regimens in the metastatic setting. (1.2)

2 DOSAGE AND ADMINISTRATION

- Premedication for diarrhea: When not using dose escalation, initiate loperamide with the first dose of NERLYNX and continue during the first 56 days of treatment. After day 56, use loperamide to maintain 1–2 bowel movements per day. (2.1, 2.2)
- Extended adjuvant treatment of early-stage breast cancer: 240 mg (6 tablets) given orally once daily, with food, continuously until disease recurrence or for up to one year. (2.2)
- Advanced or metastatic breast cancer: 240 mg (6 tablets) given orally once daily with food on Days 1–21 of a 21-day cycle plus capecitabine (750 mg/m^2given orally twice daily) on Days 1–14 of a 21-day cycle until disease progression or unacceptable toxicities. (2.2)
- Dose escalation: A two-week dose escalation for NERLYNX may also be initiated. (2.2)
- Dose interruptions and/or dose reductions are recommended based on individual safety and tolerability. (2.3)
- Hepatic impairment: Reduce starting dose to 80 mg in patients with severe hepatic impairment. (2.4)

3 DOSAGE FORMS AND STRENGTHS

Tablets: 40 mg. (3)

4 CONTRAINDICATIONS

None. (4)

5 WARNINGS AND PRECAUTIONS

- Diarrhea: Manage diarrhea through either NERLYNX dose escalation or loperamide prophylaxis (2.1, 2.2). If diarrhea occurs despite recommended prophylaxis, treat with additional antidiarrheals, fluids, and electrolytes as clinically indicated. Withhold NERLYNX in patients experiencing severe and/or persistent diarrhea. Permanently discontinue NERLYNX in patients experiencing Grade 4 diarrhea or Grade ≥2 diarrhea that occurs after maximal dose reduction. (2.3, 5.1)
- Hepatotoxicity: Monitor liver function tests monthly for the first 3 months of treatment, then every 3 months while on treatment and as clinically indicated. Withhold NERLYNX in patients experiencing Grade 3 liver abnormalities and permanently discontinue NERLYNX in patients experiencing Grade 4 liver abnormalities. (2.3, 5.2)
- Embryo-Fetal Toxicity: NERLYNX can cause fetal harm. Advise patients of potential risk to a fetus and to use effective contraception. (5.3, 8.1, 8.3)

6 ADVERSE REACTIONS

The most common adverse reactions (reported in ≥5% of patients) were:

- NERLYNX as a single agent: diarrhea, nausea, abdominal pain, fatigue, vomiting, rash, stomatitis, decreased appetite, muscle spasms, dyspepsia, AST or ALT increased, nail disorder, dry skin, abdominal distention, epistaxis, weight decreased, and urinary tract infection. (6)
- NERLYNX in combination with capecitabine: diarrhea, nausea, vomiting, decreased appetite, constipation, fatigue/asthenia, weight decreased, dizziness, back pain, arthralgia, urinary tract infection, upper respiratory tract infection, abdominal distention, renal impairment, and muscle spasms. (6)

To report SUSPECTED ADVERSE REACTIONS, contact Puma Biotechnology, Inc. at 1-844-NERLYNX (1-844-637-5969) or FDA at 1-800-FDA-1088 orwww.fda.gov/medwatch.

7 DRUG INTERACTIONS

- Gastric acid reducing agents: Avoid concomitant use with proton pump inhibitors. Separate NERLYNX by at least 2 hours before or 10 hours after H2-receptor antagonists. Or separate NERLYNX by at least 3 hours after antacids. (2.5, 7.1)
- Strong CYP3A4 inhibitors: Avoid concomitant use. (7.1)
- P-gp and moderate CYP3A4 dual inhibitors: Avoid concomitant use. (7.1)
- Strong or moderate CYP3A4 inducers: Avoid concomitant use. (7.1)
- Certain P-gp substrates: Monitor for adverse reactions of P-gp substrates for which minimal concentration change may lead to serious adverse reactions when used concomitantly with NERLYNX. (7.2)

8 USE IN SPECIFIC POPULATIONS

Lactation: Advise women not to breastfeed. (8.2)

FULL PRESCRIBING INFORMATION

1 INDICATIONS AND USAGE

1.1 Extended Adjuvant Treatment of Early-Stage Breast Cancer

NERLYNX as a single agent is indicated for the extended adjuvant treatment of adult patients with early-stage human epidermal growth factor receptor 2 (HER2)-positive breast cancer, to follow adjuvant trastuzumab based therapy [see Clinical Studies (14.1)] .

1.2 Advanced or Metastatic Breast Cancer

NERLYNX in combination with capecitabine is indicated for the treatment of adult patients with advanced or metastatic HER2-positive breast cancer who have received two or more prior anti-HER2 based regimens in the metastatic setting [see Clinical Studies (14.2)] .

2 DOSAGE AND ADMINISTRATION

2.1 Premedication for Diarrhea

When not using dose escalation [see Dosage and Administration (2.2)], administer antidiarrheal prophylaxis during the first 56 days of treatment and initiate with the first dose of NERLYNX [see Warnings and Precautions (5.1) and Adverse Reactions (6.1)] .

Instruct patients to take loperamide as directed in Table 1. Titrate loperamide to 1–2 bowel movements per day.

Table 1: Loperamide Prophylaxis
Time on NERLYNX | Loperamide Dose and Frequency
Weeks 1–2 (days 1–14) | 4 mg three times daily
Weeks 3–8 (days 15–56) | 4 mg twice daily
Weeks 9–Discontinuation of NERLYNX | 4 mg as needed, not to exceed 16 mg per day; titrate dosing to achieve 1–2 bowel movements per day

If diarrhea occurs despite prophylaxis, treat with additional antidiarrheals, fluids and electrolytes as clinically indicated. NERLYNX dose interruptions and dose reductions may also be required to manage diarrhea [see Dosage and Administration (2.3)] .

2.2 Recommended Dose and Schedule

Extended Adjuvant Treatment of Early-Stage Breast Cancer

The recommended dose of NERLYNX is 240 mg (six tablets) given orally once daily, with food, continuously until disease recurrence or for up to one year.

Advanced or Metastatic Breast Cancer

The recommended dose of NERLYNX is 240 mg (six tablets) given orally once daily with food on Days 1–21 of a 21-day cycle plus capecitabine (750 mg/m^2given orally twice daily) on Days 1–14 of a 21-day cycle until disease progression or unacceptable toxicities.

Dose Escalation

A two-week dose escalation for NERLYNX may be considered instead of starting at the 240 mg daily dose for patients with early-stage breast cancer and metastatic breast cancer, as described in Table 2 [see Warnings and Precautions (5.1) and Adverse Reactions (6.1)] .

Table 2: NERLYNX Dose Escalation and Treatment Schedule
Time on NERLYNX | NERLYNX Dose
Week 1 (days 1–7) | 120 mg daily (three 40 mg tablets)
Week 2 (days 8–14) | 160 mg daily (four 40 mg tablets)
Week 3 and onwards | 240 mg daily (six 40 mg tablets, recommended dose)

If diarrhea occurs, treat with antidiarrheal medications, fluids, and electrolytes as clinically indicated. NERLYNX dose interruptions and dose reductions may also be required to manage diarrhea [see Dosage and Administration (2.3)] .

Administration Instructions

Instruct patients to take NERLYNX at approximately the same time every day. NERLYNX tablets should be swallowed whole (tablets should not be chewed, crushed, or split prior to swallowing).

If a patient misses a dose, do not replace missed dose, and instruct the patient to resume NERLYNX with the next scheduled daily dose.

2.3 Dosage Modifications for Adverse Reactions

NERLYNX dose modification is recommended based on individual safety and tolerability. Management of some adverse reactions may require dose interruption and/or dose reduction as shown in Table 3to Table 6.

Discontinue NERLYNX for patients with adverse reactions that fail to recover to Grade 0–1 or baseline, with toxicities that result in a treatment delay >3 weeks, or if unable to tolerate 120 mg daily. Additional clinical situations may result in dose adjustments as clinically indicated (e.g., intolerable toxicities, persistent Grade 2 adverse reactions, etc.).

When NERLYNX is used in combination with capecitabine, refer to the capecitabine prescribing information for dose modifications of capecitabine.

Table 3: NERLYNX Monotherapy Dose Modifications for Adverse Reactions
Dose Level | NERLYNX Dose
Recommended starting dose | 240 mg daily (six 40 mg tablets)
First dose reduction | 200 mg daily (five 40 mg tablets)
Second dose reduction | 160 mg daily (four 40 mg tablets)
Third dose reduction | 120 mg daily (three 40 mg tablets)

Table 4: Recommended Dosage Modifications for Adverse Reactions with NERLYNX Monotherapy
Adverse Reaction | Severity† | Action/Dose Modification
Diarrhea [see Warnings and Precautions (5.1)] | - Grade 1 diarrhea [increase of <4 stools per day over baseline] - Grade 2 diarrhea [increase of 4–6 stools per day over baseline] lasting ≤5 days - Grade 3 diarrhea [increase of ≥7 stools per day over baseline; incontinence; hospitalization indicated; limiting self-care activities of daily living] lasting ≤2 days | - Adjust antidiarrheal treatment - Diet modifications - Fluid intake of ~2 L/day should be maintained to avoid dehydration - Once event resolves to ≤Grade 1 or baseline, start loperamide 4 mg with each subsequent NERLYNX administration
Diarrhea [see Warnings and Precautions (5.1)] | - Any grade with complicated features* - Grade 2 diarrhea lasting longer than 5 days‡ - Grade 3 diarrhea lasting longer than 2 days‡ | - Interrupt NERLYNX treatment - Diet modifications - Fluid intake of ~2 L/day should be maintained to avoid dehydration - If diarrhea resolves to ≤Grade 1 in one week or less, then resume NERLYNX treatment at the same dose - If diarrhea resolves to ≤Grade 1 in longer than one week, then resume NERLYNX treatment at reduced dose (see Table 3) - Once event resolves to ≤Grade 1 or baseline, start loperamide 4 mg with each subsequent NERLYNX administration
Diarrhea [see Warnings and Precautions (5.1)] | - Grade 4 diarrhea [life-threatening consequences; urgent intervention indicated] | - Permanently discontinue NERLYNX treatment
Diarrhea [see Warnings and Precautions (5.1)] | - Diarrhea recurs to Grade 2 or higher at 120 mg per day | - Permanently discontinue NERLYNX treatment
Hepatotoxicity [see Warnings and Precautions (5.2)] | - Grade 3 ALT or AST (>5–20× ULN) OR - Grade 3 bilirubin (>3–10× ULN) | - Hold NERLYNX until recovery to ≤Grade 1 - Evaluate alternative causes - Resume NERLYNX at the next lower dose level if recovery to ≤Grade 1 occurs within 3 weeks. If Grade 3 ALT or AST, or bilirubin occurs again despite one dose reduction, permanently discontinue NERLYNX.
Hepatotoxicity [see Warnings and Precautions (5.2)] | - Grade 4 ALT or AST (>20× ULN) OR - Grade 4 bilirubin (>10× ULN) | - Permanently discontinue NERLYNX - Evaluate alternative causes
Other [see Adverse Reactions (6.1)] | - Grade 3 | - Hold NERLYNX until recovery to ≤Grade 1 or baseline within 3 weeks of stopping treatment. Then resume NERLYNX at the next lower dose level.
Other [see Adverse Reactions (6.1)] | - Grade 4 | - Discontinue NERLYNX permanently
ALT=Alanine Aminotransferase; AST=Aspartate Aminotransferase; ULN=Upper Limit Normal
† Per CTCAE v4.0
* Complicated features include dehydration, fever, hypotension, renal failure, or Grade 3 or 4 neutropenia.
‡ Despite being treated with optimal medical therapy

Table 5: NERLYNX in Combination with Capecitabine Dose Modifications for Adverse Reactions
Dose Level | NERLYNX Dose
Recommended starting dose | 240 mg daily (six 40 mg tablets)
First dose reduction | 160 mg daily (four 40 mg tablets)
Second dose reduction | 120 mg daily (three 40 mg tablets)

Table 6: Recommended Dosage Modifications for Adverse Reactions with NERLYNX in Combination with Capecitabine
Adverse Reaction | Severity† | Action/Dose Modification
Diarrhea [see Warnings and Precautions (5.1)] | - Grade 1 Diarrhea [Increase of <4 stools per day over baseline] - Grade 2 Diarrhea [Increase of 4–6 stools per day over baseline] lasting ≤5 days - Grade 3 Diarrhea [Increase of ≥7 stools per day over baseline; incontinence; hospitalization indicated; limiting self-care and activities of daily living] lasting ≤2 days | - Adjust antidiarrheal treatment - Continue NERLYNX and capecitabine at full doses - Diet modifications - Fluid intake of ~2 L/day should be maintained to avoid dehydration - Once the event resolves to Grade ≤1 or baseline, start loperamide 4 mg with each subsequent NERLYNX administration
Diarrhea [see Warnings and Precautions (5.1)] | - Persisting and intolerable Grade 2 Diarrhea lasting >5 days - Grade 3 Diarrhea lasting >2 days - Grade 4 Diarrhea [Life-threatening consequences; urgent intervention indicated] | - Adjust antidiarrheal treatment - Hold NERLYNX and capecitabine until recovery to Grade ≤1 or baseline - Diet modifications - Fluid intake of ~2 L/day should be maintained intravenously, if needed - If recovery occurs: - ≤1 week after withholding treatment, resume same doses of NERLYNX and capecitabine - Within 1–3 weeks after withholding treatment, reduce NERLYNX dose to 160 mg and maintain the same dose of capecitabine - If event occurs a second time and the NERLYNX dose has not already been decreased, reduce NERLYNX dose to 160 mg (maintain the same dose of capecitabine). If NERLYNX dose has already been reduced, then reduce the dose of capecitabine to 550 mg/m^2 given twice dailya(maintain the same dose of NERLYNX). - If subsequent events occur, reduce the dose of NERLYNX or capecitabine to the next lower dose level in an alternate fashion (i.e., reduce capecitabine to 375 mg/m^2 given twice dailyaif NERLYNX was previously reduced, or reduce NERLYNX to 120 mg if capecitabine was previously reduced) - Once the event resolves to Grade ≤1 or baseline, start loperamide 4 mg with each subsequent NERLYNX administration
Hepatotoxicity [see Warnings and Precautions (5.2)] | - Grade 3 ALT or AST (>5–20× ULN) OR - Grade 3 bilirubin (>3–10× ULN) | - Hold NERLYNX until recovery to ≤Grade 1 - Evaluate alternative causes - Resume NERLYNX at the next lower dose level if recovery to ≤Grade 1 occurs within 3 weeks. If Grade 3 ALT or AST, or bilirubin occurs again despite one dose reduction, permanently discontinue NERLYNX.
Hepatotoxicity [see Warnings and Precautions (5.2)] | - Grade 4 ALT or AST (>20× ULN) OR - Grade 4 bilirubin (>10× ULN) | - Permanently discontinue NERLYNX - Evaluate alternative causes
Other [see Adverse Reactions (6.1)] | - Grade 3 | - Hold NERLYNX until recovery to Grade ≤1 or baseline within 3 weeks of stopping treatment. Then resume NERLYNX at the next lower dose level.
Other [see Adverse Reactions (6.1)] | - Grade 4 | - Discontinue NERLYNX permanently
ALT=Alanine Aminotransferase; AST=Aspartate Aminotransferase; ULN=Upper Limit Normal
† Per CTCAE v4.0
aSince capecitabine is provided as 150 mg or 500 mg tablets, it is recommended that the capecitabine dose reduction(s) is(are) rounded down to the nearest 500 mg or multiple of 150 mg for the twice daily dose. If the patient's body surface area is >2.0, the standard of care for the study center can be utilized for capecitabine mg/m^2dosing.

2.4 Dosage Modifications for Hepatic Impairment

Reduce the NERLYNX starting dose to 80 mg in patients with severe hepatic impairment (Child Pugh C). No dose modifications are recommended for patients with mild to moderate hepatic impairment (Child Pugh A or B) [see Use in Specific Populations (8.6) and Clinical Pharmacology (12.3)] .

2.5 Dosage Modifications for Gastric Acid Reducing Agents

Proton pump inhibitors (PPI):Avoid concomitant use with NERLYNX [see Drug Interactions (7.1)] .

H 2-receptor antagonists:Take NERLYNX at least 2 hours before the next dose of the H2-receptor antagonist or 10 hours after the H2-receptor antagonist [see Drug Interactions (7.1)] .

Antacids:Separate dosing of NERLYNX by 3 hours after antacids [see Drug Interactions (7.1)] .

3 DOSAGE FORMS AND STRENGTHS

Tablets: 40 mg neratinib (equivalent to 48.31 mg of neratinib maleate).

Film-coated, red, oval shaped and debossed with 'W104' on one side and plain on the other side.

4 CONTRAINDICATIONS

None.

5 WARNINGS AND PRECAUTIONS

5.1 Diarrhea

Severe diarrhea and sequelae, such as dehydration, hypotension, and renal failure occurred during treatment with NERLYNX. Diarrhea was reported in 95% of NERLYNX-treated patients in ExteNET, a randomized placebo-controlled trial in the extended adjuvant setting who were not required to receive antidiarrheal prophylaxis. In the NERLYNX arm, Grade 3 diarrhea occurred in 40% and Grade 4 diarrhea occurred in 0.1% of patients. The majority of patients (93%) had diarrhea in the first month of treatment, the median time to first onset of Grade ≥3 diarrhea was 8 days (range, 1–350), and the median cumulative duration of Grade ≥3 diarrhea was 5 days (range, 1–139) [see Adverse Reactions (6.1)] .

Diarrhea was reported in 83% of NERLYNX plus capecitabine treated patients in NALA, a randomized placebo-controlled trial in the metastatic breast cancer setting who were required to receive anti-diarrheal prophylaxis in the first 21-day cycle. The majority of patients (70%) had diarrhea in the first 21 days of treatment, the median time to first onset of Grade ≥3 diarrhea was 11 days (range, 2–728) and the median cumulative duration of Grade ≥3 diarrhea was 3 days (range, 1–21). In the NERLYNX plus capecitabine arm, Grade 3 diarrhea occurred in 24% of patients [see Adverse Reactions (6.1)] .

Antidiarrheal prophylaxis has been shown to lower the incidence and severity of diarrhea. Instruct patients to initiate antidiarrheal prophylaxis with loperamide along with the first dose of NERLYNX and continue during the first 56 days of treatment; after day 56, titrate dose to achieve 1–2 bowel movements per day and not to exceed 16 mg loperamide per day [see Dosage and Administration (2.1)]. Consider adding other agents to loperamide as clinically indicated [see Adverse Reactions (6.1)] .

Alternatively, a 2-week NERLYNX dose escalation approach prior to initiation of the recommended treatment regimen with NERLYNX can also be considered for diarrhea management [see Dosage and Administration (2.2)]. For patients who used NERLYNX dose escalation, the median time to first onset of Grade ≥3 diarrhea was 45 days (range, 15–132) and the median cumulative duration of Grade ≥3 diarrhea was 2.5 days (range, 1–6). Grade 3 diarrhea occurred in 13% of patients who used NERLYNX dose escalation [see Adverse Reactions (6.1)].

Monitor patients for diarrhea and treat with additional antidiarrheals as needed. When severe diarrhea with dehydration occurs, administer fluid and electrolytes as needed, interrupt NERLYNX, and reduce subsequent doses [see Dosage and Administration (2.3)]. Perform stool cultures as clinically indicated to exclude infectious causes of Grade 3 or 4 diarrhea or diarrhea of any grade with complicating features (dehydration, fever, neutropenia).

5.2 Hepatotoxicity

NERLYNX has been associated with hepatotoxicity characterized by increased liver enzymes. In ExteNET, 10% of patients experienced an alanine aminotransferase (ALT) increase ≥2× ULN, 5% of patients experienced an aspartate aminotransferase (AST) increase ≥2× ULN, and 1.7% of patients experienced an AST or ALT increase >5× ULN (≥Grade 3). Hepatotoxicity or increases in liver transaminases led to drug discontinuation in 1.7% of NERLYNX-treated patients.

In the NALA study, in NERLYNX and capecitabine-treated patients, 7% experienced an ALT or AST increase >3× ULN, 2% experienced an ALT or AST increase >5× ULN, 7% experienced a bilirubin increase >1.5× ULN, and 1.3% experienced a bilirubin increase >3× ULN. Hepatotoxicity or increases in liver transaminases led to drug discontinuation in 0.3% of NERLYNX and capecitabine-treated patients.

Total bilirubin, AST, ALT, and alkaline phosphatase should be measured prior to starting treatment with NERLYNX monthly for the first 3 months of treatment, then every 3 months while on treatment and as clinically indicated. These tests should also be performed in patients experiencing Grade 3 diarrhea or any signs or symptoms of hepatotoxicity, such as worsening of fatigue, nausea, vomiting, right upper quadrant tenderness, fever, rash, or eosinophilia [see Dosage and Administration (2.3) and Adverse Reactions (6.1)] .

5.3 Embryo-Fetal Toxicity

Based on findings from animal studies and its mechanism of action, NERLYNX can cause fetal harm when administered to a pregnant woman. In animal reproduction studies, administration of neratinib to pregnant rabbits during organogenesis caused abortions, embryo-fetal death, and fetal abnormalities in rabbits at maternal AUCs approximately 0.2 times the AUC in patients receiving the recommended dose. Advise pregnant women of the potential risk to a fetus. Advise females of reproductive potential to use effective contraception during treatment and for at least 1 month after the last dose. [see Use in Specific Populations (8.1, 8.3) and Clinical Pharmacology (12.1)] .

6 ADVERSE REACTIONS

The following clinically significant adverse reactions are described elsewhere in the labeling:

- Diarrhea [see Warnings and Precautions (5.1)]
- Hepatotoxicity [see Warnings and Precautions (5.2)]

6.1 Clinical Trials Experience

Because clinical trials are conducted under widely varying conditions, adverse reaction rates observed in the clinical trials of a drug cannot be directly compared to rates in the clinical trials of another drug and may not reflect the rates observed in practice.

Extended Adjuvant Treatment of Early-Stage Breast Cancer

ExteNET

The data described below reflect the safety data of NERLYNX as a single agent in ExteNET, a multicenter, randomized, double-blind, placebo-controlled study of NERLYNX within 2 years after completion of adjuvant treatment with trastuzumab-based therapy in women with HER2-positive early-stage breast cancer. Patients who received NERLYNX in this trial were not required to receive any prophylaxis with antidiarrheal agents to prevent the NERLYNX-related diarrhea. Patients were treated with 240 mg of NERLYNX given orally once daily with food, continuously until disease recurrence or for up to one year. The median duration of treatment was 11.6 months in the NERLYNX arm and 11.8 months in the placebo arm. The median age was 52 years (60% were ≥50 years old, 12% were ≥65 years old); 81% were Caucasian, 3% Black or African American, 14% Asian, and 3% other. A total of 1408 patients were treated with NERLYNX.

NERLYNX dose reduction due to an adverse reaction of any grade occurred in 31% of patients receiving NERLYNX compared to 2.6% of patients receiving placebo. Permanent discontinuation due to any adverse reaction was reported in 28% of NERLYNX-treated patients. The most common adverse reaction leading to discontinuation was diarrhea, accounting for 17% of NERLYNX-treated patients.

The most common adverse reactions (≥5%) were diarrhea, nausea, abdominal pain, fatigue, vomiting, rash, stomatitis, decreased appetite, muscle spasms, dyspepsia, AST or ALT increased, nail disorder, dry skin, abdominal distention, epistaxis, weight decreased, and urinary tract infection. The most frequently reported Grade 3 or 4 adverse reactions were diarrhea, vomiting, nausea, and abdominal pain.

Serious adverse reactions in the NERLYNX arm included diarrhea (1.6%), vomiting (0.9%), dehydration (0.6%), cellulitis (0.4%), renal failure (0.4%), erysipelas (0.4%), ALT increased (0.3%), AST increased (0.3%), nausea (0.3%), fatigue (0.2%), and abdominal pain (0.2%).

Table 7summarizes the adverse reactions in ExteNET.

Table 7: Adverse Reactions Reported in ≥2% of NERLYNX-Treated Patients in ExteNET
System Organ Class (Preferred Term) | NERLYNX n=1408 |  |  | Placebo n=1408
System Organ Class (Preferred Term) | All Grades (%) | Grade 3 (%) | Grade 4 (%) | All Grades (%) | Grade 3 (%) | Grade 4 (%)
Gastrointestinal Disorders
Diarrhea | 95 | 40 | 0.1 | 35 | 2 | 0
Nausea | 43 | 2 | 0 | 22 | 0.1 | 0
Abdominal pain* | 36 | 2 | 0 | 15 | 0.4 | 0
Vomiting | 26 | 3 | 0 | 8 | 0.4 | 0
Stomatitis† | 14 | 0.6 | 0 | 6 | 0.1 | 0
Dyspepsia | 10 | 0.4 | 0 | 4 | 0 | 0
Abdominal distension | 5 | 0.3 | 0 | 3 | 0 | 0
Dry mouth | 3 | 0.1 | 0 | 2 | 0 | 0
General Disorders and Administration Site Conditions
Fatigue | 27 | 2 | 0 | 20 | 0.4 | 0
Hepatobiliary Disorders
Alanine aminotransferase increased | 9 | 1 | 0.2 | 3 | 0.2 | 0
Aspartate aminotransferase increased | 7 | 0.5 | 0.2 | 3 | 0.3 | 0
Infections and Infestations
Urinary tract infection | 5 | 0.1 | 0 | 2 | 0 | 0
Investigations
Weight decreased | 5 | 0.1 | 0 | 0.5 | 0 | 0
Metabolism and Nutrition Disorders
Decreased appetite | 12 | 0.2 | 0 | 3 | 0 | 0
Dehydration | 4 | 0.9 | 0.1 | 0.4 | 0.1 | 0
Musculoskeletal and Connective Tissue Disorders
Muscle spasms | 11 | 0.1 | 0 | 3 | 0.1 | 0
Respiratory, Thoracic and Mediastinal Disorders
Epistaxis | 5 | 0 | 0 | 1 | 0.1 | 0
Skin and Subcutaneous Tissue Disorders
Rash‡ | 18 | 0.6 | 0 | 9 | 0 | 0
Dry skin | 6 | 0 | 0 | 2 | 0 | 0
Nail disorder§ | 8 | 0.3 | 0 | 2 | 0 | 0
Skin fissures | 2 | 0.1 | 0 | 0.1 | 0 | 0
* Includes abdominal pain, abdominal pain upper, and abdominal pain lower
† Includes stomatitis, aphthous stomatitis, mouth ulceration, oral mucosal blistering, mucosal inflammation, oropharyngeal pain, oral pain, glossodynia, glossitis, and cheilitis
‡ Includes rash, rash erythematous, rash follicular, rash generalized, rash pruritic, rash pustular, rash maculo-papular, rash papular, dermatitis, dermatitis acneiform, and toxic skin eruption
§ Includes nail disorder, paronychia, onychoclasis, nail discoloration, nail toxicity, nail growth abnormal, and nail dystrophy

Advanced or Metastatic Breast Cancer

NALA

The data described below reflect the safety data of NERLYNX plus capecitabine in NALA, a randomized, multicenter, multinational, open-label, active-controlled study of HER2-positive metastatic breast cancer in patients, with or without brain metastases, who have received two or more prior anti HER2-based regimens in the metastatic setting.

Patients were treated with NERLYNX 240 mg orally once daily Days 1–21 of a 21-day cycle in combination with capecitabine (750 mg/m^2given orally twice daily) Days 1–14 of a 21-day cycle, or lapatinib 1250 mg orally once daily Days 1–21 of a 21-day cycle in combination with capecitabine (1000 mg/m^2given orally twice daily) Days 1–14 of a 21-day cycle until disease progression. The median duration of treatment was 5.7 months in the NERLYNX plus capecitabine arm and 4.4 months in the lapatinib plus capecitabine arm.

NERLYNX dose reduction due to an adverse reaction of any grade occurred in 10% of patients receiving NERLYNX plus capecitabine. Permanent discontinuation due to any adverse reaction was reported in 14% of NERLYNX plus capecitabine treated patients. The most common adverse reactions leading to discontinuation were vomiting (3.6%), diarrhea (2.6%), nausea (2.6%), and palmar-plantar erythrodysaesthesia syndrome (2.3%) of NERLYNX plus capecitabine-treated patients.

The most common adverse reactions of any grade (≥5%) in the NERLYNX plus capecitabine arm were diarrhea, nausea, vomiting, decreased appetite, constipation, fatigue/asthenia, weight decreased, dizziness, back pain, arthralgia, urinary tract infection, upper respiratory tract infection, abdominal distention, renal impairment, and muscle spasms. The most frequently reported Grade 3 or 4 adverse reactions were diarrhea, nausea, vomiting, fatigue, and decreased appetite.

Serious adverse reactions ≥2% in the NERLYNX plus capecitabine arm included diarrhea (7%), vomiting (3%), nausea (2.3%), and acute kidney injury (2.3%).

Table 8summarizes the adverse reactions in NALA.

Table 8: Adverse Reactions Reported in ≥2% of NERLYNX-Treated Patients in Combination with Capecitabine in NALA
System Organ Class (Preferred Term) | NERLYNX + Capecitabine n=303 |  |  | Lapatinib + Capecitabine n=311
System Organ Class (Preferred Term) | All Grades (%) | Grade 3 (%) | Grade 4 (%) | All Grades (%) | Grade 3 (%) | Grade 4 (%)
Gastrointestinal Disorders
Diarrhea | 83 | 25 | 0 | 66 | 13 | 0
Nausea | 53 | 4.3 | 0 | 42 | 2.9 | 0
Vomiting | 46 | 4 | 0 | 31 | 1.9 | 0
Constipation | 31 | 1 | 0 | 13 | 0 | 0
Abdominal distension | 8 | 0.3 | 0 | 3.2 | 0.6 | 0
General Disorders and Administration Site Conditions
Fatigue/asthenia | 45 | 6 | 0 | 40 | 4.5 | 0
Malaise | 4.3 | 0 | 0 | 2.3 | 0.3 | 0
Influenza like illness | 4 | 0 | 0 | 1.3 | 0 | 0
Infections and Infestations
Urinary tract infection | 9 | 0.7 | 0 | 4.2 | 0.6 | 0
Upper respiratory tract infection | 8 | 0.3 | 0 | 4.5 | 0.3 | 0
Investigations
Weight decreased | 20 | 0.3 | 0 | 13 | 0.6 | 0
Metabolism and Nutrition Disorders
Decreased appetite | 35 | 2.6 | 0 | 22 | 2.3 | 0
Musculoskeletal and Connective Tissue Disorders
Back pain | 10 | 0.3 | 0 | 8 | 0.3 | 0
Arthralgia | 10 | 0 | 0 | 6 | 1 | 0
Muscle spasms | 5 | 0 | 0 | 1.9 | 0 | 0
Nervous System Disorder
Dizziness | 14 | 0.3 | 0 | 10 | 0.6 | 0
Renal and urinary disorders
Renal impairment* | 7 | 2 | 0.3 | 1 | 0 | 0.3
Dysuria | 4.6 | 0 | 0 | 1.9 | 0 | 0
* Renal impairment includes acute kidney injury, blood creatinine increased, renal failure, and renal impairment.

Management of Diarrhea

CONTROL

The CONTROL (NCT02400476) study was a multicenter, open-label, multi-cohort trial evaluating patients with early-stage HER2-positive breast cancer treated with NERLYNX 240 mg daily for up to one year receiving loperamide prophylaxis with additional anti-diarrheal treatment as needed or NERLYNX dose escalation with loperamide as needed. All patients in the prophylaxis cohort received loperamide 4 mg loading dose, followed by 4 mg three times a day from days 1-14, followed by 4 mg twice a day on days 15-56, followed by loperamide as needed through 1 year of treatment with NERLYNX [see Dosage and Administration (2.1)]. All patients in the dose escalation cohort received NERLYNX 120 mg for Week 1, followed by NERLYNX 160 mg for Week 2, followed by NERLYNX 240 mg for Week 3 and thereafter [see Dosage and Administration (2.2)] .

Table 9summarizes the diarrhea adverse reactions for NERLYNX with loperamide prophylaxis and NERLYNX dose escalation.

Table 9: Diarrhea in Patients Treated with NERLYNX with Antidiarrheal Prophylaxis or Dose Escalation
 | Loperamide Prophylaxis n=109 | NERLYNX Dose Escalation n=60
Duration of Treatment, months
Median | 11.8 | 12.0
Range | 0.1, 12.8 | 0.2, 12.4
Dose Intensity, mg per day
Median | 234 | 230
Range | 46, 240 | 32, 236
Incidence of Diarrhea, %
Any Grade | 78 | 98
Grade 2 | 25 | 45
Grade 3 | 32 | 13
Action Taken, %
Discontinuation due to diarrhea | 18 | 3.3

7 DRUG INTERACTIONS

7.1 Effect of Other Drugs on NERLYNX

Table 10includes drug interactions that affect the pharmacokinetics of neratinib.

Table 10: Drug Interactions that Affect NERLYNX
Gastric Acid Reducing Agents
Clinical Impact | Concomitant use of NERLYNX with a proton pump inhibitor (PPI), H2-receptor antagonist, or antacid may decrease neratinib AUC [see Clinical Pharmacology (12.3)], which may reduce NERLYNX activity.
Prevention or Management [see Dosage and Administration (2.5)] | Avoid concomitant use of PPIs.
Prevention or Management [see Dosage and Administration (2.5)] | Separate administration of NERLYNX at least 2 hours before or 10 hours after the H2-receptor antagonist dose.
Prevention or Management [see Dosage and Administration (2.5)] | Separate administration of NERLYNX by at least 3 hours after antacids.
Strong CYP3A4 Inhibitors
Clinical Impact | Concomitant use of NERLYNX with a strong CYP3A4 inhibitor increased neratinib Cmaxand AUC [see Clinical Pharmacology (12.3)] , which may increase the risk of NERLYNX toxicity.
Prevention or Management | Avoid concomitant use of NERLYNX with strong CYP3A4 inhibitors.
P-gp and Moderate CYP3A4 Dual Inhibitors
Clinical Impact | Concomitant use of NERLYNX with a P-gp and moderate CYP3A4 dual inhibitor may increase neratinib Cmaxand AUC [see Clinical Pharmacology (12.3)] , which may increase the risk of NERLYNX toxicity.
Prevention or Management | Avoid concomitant use of NERLYNX with P-gp and moderate CYP3A4 dual inhibitors.
Strong or Moderate CYP3A4 Inducers
Clinical Impact | Concomitant use of NERLYNX with a strong CYP3A4 inducer reduced neratinib Cmaxand AUC [see Clinical Pharmacology (12.3)] , which may reduce NERLYNX activity.
Prevention or Management | Avoid concomitant use of NERLYNX with strong or moderate CYP3A4 inducers.
AUC=Area Under Curve; Cmax=Maximum Concentration

7.2 Effect of NERLYNX on Other Drugs

Certain P-glycoprotein (P-gp) Substrates

Concomitant use of NERLYNX increased concentrations of a P-gp substrate [see Clinical Pharmacology (12.3)] , which may increase the risk of adverse reactions of these substrates. Monitor for adverse reactions of certain P-gp substrates for which minimal concentration changes may lead to serious adverse reactions.

8 USE IN SPECIFIC POPULATIONS

8.1 Pregnancy

Risk Summary

Based on findings from animal studies and the mechanism of action, NERLYNX can cause fetal harm when administered to a pregnant woman [see Clinical Pharmacology (12.1)] .

There are no available data in pregnant women to inform the drug-associated risk. In animal reproduction studies, administration of neratinib to pregnant rabbits during organogenesis resulted in abortions, embryo-fetal death and fetal abnormalities in rabbits at maternal exposures (AUC) approximately 0.2 times exposures in patients at the recommended dose (see Data). Advise pregnant women of the potential risk to a fetus.

The background risk of major birth defects and miscarriage for the indicated population is unknown. However, the background risk of major birth defects is 2%–4% and of miscarriage is 15%–20% of clinically recognized pregnancies in the U.S. general population.

Data

Animal Data

In a fertility and early embryonic development study in female rats, neratinib was administered orally for 15 days before mating to Day 7 of pregnancy, which did not cause embryonic toxicity at doses up to 12 mg/kg/day in the presence of maternal toxicity. A dose of 12 mg/kg/day in rats is approximately 0.5 times the maximum recommended dose of 240 mg/day in patients on a mg/m^2basis.

In an embryo-fetal development study in rats, pregnant animals received oral doses of neratinib up to 15 mg/kg/day during the period of organogenesis. No effects on embryo-fetal development or survival were observed. Maternal toxicity was evident at 15 mg/kg/day (approximately 0.6 times the AUC in patients receiving the maximum recommended dose of 240 mg/day).

In an embryo-fetal development study in rabbits, pregnant animals received oral doses of neratinib up to 9 mg/kg/day during the period of organogenesis. Administration of neratinib at doses ≥6 mg/kg/day resulted in maternal toxicity, abortions, and embryo-fetal death (increased resorptions). Neratinib administration resulted in increased incidence of fetal gross external (domed head), soft tissue (dilation of the brain ventricles and ventricular septal defect), and skeletal (misshapen anterior fontanelles and enlarged anterior and/or posterior fontanelles) abnormalities at ≥3 mg/kg/day. The AUC(0-t)at 6 mg/kg/day and 9 mg/kg/day in rabbits were approximately 0.5 and 0.8 times, respectively, the AUCs in patients receiving the maximum recommended dose of 240 mg/day.

In a peri- and postnatal development study in rats, oral administration of neratinib from gestation day 7 until lactation day 20 resulted in maternal toxicity at ≥10 mg/kg/day (approximately 0.4 times the maximum recommended dose of 240 mg/day in patients on a mg/m^2basis) including decreased body weights, body weight gains, and food consumption. Effects on long-term memory were observed in male offspring at maternal doses ≥5 mg/kg/day (approximately 0.2 times the maximum recommended dose of 240 mg/day in patients on a mg/m^2basis).

8.2 Lactation

Risk Summary

No data are available regarding the presence of neratinib or its metabolites in human milk or its effects on the breastfed infant or on milk production. Because of the potential for serious adverse reactions in breastfed infants from NERLYNX, advise lactating women not to breastfeed while taking NERLYNX and for at least 1 month after the last dose.

8.3 Females and Males of Reproductive Potential

Pregnancy

Based on animal studies, NERLYNX can cause fetal harm when administered to a pregnant woman [see Use in Specific Populations (8.1)] . Females of reproductive potential should have a pregnancy test prior to starting treatment with NERLYNX.

Contraception

Females

Based on animal studies, NERLYNX can cause fetal harm when administered to a pregnant woman [see Use in Specific Populations (8.1)] . Advise females of reproductive potential to use effective contraception during treatment with NERLYNX and for at least 1 month after the last dose.

Males

Based on findings in animal reproduction studies, advise male patients with female partners of reproductive potential to use effective contraception during treatment and for 3 months after the last dose of NERLYNX [see Use in Specific Populations (8.1)] .

8.4 Pediatric Use

The safety and efficacy of NERLYNX in pediatric patients has not been established.

8.5 Geriatric Use

In the ExteNET trial, in the NERLYNX arm; 1236 patients were <65 years, 172 patients were ≥65 years, of whom 25 patients were 75 years or older. There was a higher frequency of treatment discontinuations due to adverse reactions in the ≥65 years age group than in the <65 years age group; in the NERLYNX arm, the percentages were 45% compared with 25%, respectively, and in the placebo arm 6% and 5%, respectively. The incidence of serious adverse reactions in the NERLYNX arm vs placebo arm was 7% vs 6% (<65 years old) and 10% vs 8% (≥65 years old). The serious adverse reactions most frequently reported in the ≥65 years old group were vomiting (2.3%), diarrhea (1.7%), renal failure (1.7%), and dehydration (1.2%).

In the NALA trial, in the NERLYNX plus capecitabine arm; 242 patients were <65 years, 61 patients were ≥65 years, of whom 12 patients were 75 years or older. The incidence of serious adverse reactions in the NERLYNX plus capecitabine arm in the ≥65 years age group was 36% and in the <65 years age group was 34%. The serious adverse reactions most frequently reported in the ≥65 years age group were diarrhea (16%), acute kidney injury (8%), and dehydration (7%). No overall differences in effectiveness were observed between patients ≥65 years old and patients <65 years old.

8.6 Hepatic Impairment

No dosage modifications are recommended for patients with mild to moderate hepatic impairment (Child Pugh A or B).

Neratinib clearance is reduced, and Cmaxand AUC increase in patients with severe, pre-existing hepatic impairment (Child Pugh C). Reduce the NERLYNX dosage for patients with severe hepatic impairment [see Dosage and Administration (2.4) and Clinical Pharmacology (12.3)] .

10 OVERDOSAGE

There is no specific antidote, and the benefit of hemodialysis in the treatment of NERLYNX overdose is unknown. In the event of an overdose, administration should be withheld and general supportive measures undertaken.

In the clinical trial setting, a limited number of patients reported overdose. The adverse reactions experienced by these patients were diarrhea, nausea, vomiting, and dehydration. The frequency and severity of gastrointestinal disorders (diarrhea, abdominal pain, nausea, and vomiting) appear to be dose related.

11 DESCRIPTION

NERLYNX (neratinib) immediate release, film-coated tablets for oral administration contain 40 mg of neratinib, equivalent to 48.31 mg neratinib maleate. Neratinib is a member of the 4-anilino quinolidine class of protein kinase inhibitors. The molecular formula for neratinib maleate is C30H29ClN6O3•C4H4O4and the molecular weight is 673.11 Daltons. The chemical name is (E)-N-{4-[3-chloro-4-(pyridin-2-yl methoxy)anilino]-3-cyano-7-ethoxyquinolin-6-yl}-4-(dimethylamino)but-2-enamide maleate, and its structural formula is:

Neratinib maleate is an off-white to yellow powder with pKas of 7.65 and 4.66. The solubility of neratinib maleate increases dramatically as neratinib becomes protonated at acidic pH. Neratinib maleate is sparingly soluble at pH 1.2 (32.90 mg/mL) and insoluble at approximately pH 5.0 and above (0.08 mg/mL or less).

Inactive ingredients: Tablet Core: colloidal silicon dioxide, mannitol, microcrystalline cellulose, crospovidone, povidone, magnesium stearate, and purified water. Coating: red film coat: polyvinyl alcohol, titanium dioxide, polyethylene glycol, talc, and iron oxide red.

12 CLINICAL PHARMACOLOGY

12.1 Mechanism of Action

Neratinib is an intracellular kinase inhibitor that irreversibly binds to epidermal growth factor receptor (EGFR), HER2, and HER4. In vitro, neratinib reduces EGFR and HER2 autophosphorylation, downstream MAPK and AKT signaling pathways, and showed antitumor activity in EGFR and/or HER2 expressing carcinoma cell lines. Neratinib human metabolites M3, M6, M7 and M11 inhibited the activity of EGFR, HER2, and HER4 in vitro. In vivo, oral administration of neratinib inhibited tumor growth in mouse xenograft models with tumor cell lines expressing HER2 and EGFR.

12.2 Pharmacodynamics

Neratinib exposure-response relationships and the time course of pharmacodynamic response are unknown.

Cardiac Electrophysiology

The effect of NERLYNX on the QTc interval was evaluated in a randomized, placebo, and positive-controlled, double-blind, single-dose, crossover study in 60 healthy subjects. At 140% the therapeutic exposures of NERLYNX, there was no clinically relevant effect on the QTc interval.

12.3 Pharmacokinetics

Neratinib AUC increases in less than dose proportional manner over a daily dose range of 40 to 400 mg (0.17 to 1.7 times the maximum approved recommended dosage).

Absorption

Peak concentrations of neratinib and major active metabolites M3, M6 and M7 are reached in the range of 2 to 8 hours after oral administration.

Effect of Food

A high-fat meal (approximately 55% fat, 31% carbohydrate, and 14% protein) increased neratinib Cmaxand AUCinfby 70% (90% CI: 1.1–2.7) and 120% (90% CI: 1.4–3.5), respectively, in healthy subjects compared to fasting conditions. A standard breakfast (approximately 50% carbohydrate, 35% fat, and 15% protein) increased the Cmaxand AUCinfby 20% (90% CI: 0.97–1.42) and 10% (90% CI: 1.02–1.24), respectively, in healthy subjects [see Dosage and Administration (2.2)] .

Distribution

The mean (%CV) apparent volume of distribution at steady state (Vss/F) was 6433 (19%) L in patients. In vitro protein binding of neratinib was greater than 99%, predominantly to serum albumin and alpha-1 acid glycoprotein, and was independent of concentration.

Elimination

The mean (%CV) plasma half-life of neratinib, M3, M6, and M7 was 14.6 (38%), 21.6 (77%), 13.8 (50%) and 10.4 (33%) hours, respectively, in healthy subjects. The mean elimination half-life of neratinib ranged from 7 to 17 hours following a single oral dose in patients. The mean (%CV) CL/F after first dose and at steady state (day 21) were 216 (34%) and 281 (40%) L/hour, respectively, in patients.

Metabolism

Neratinib is metabolized primarily in the liver by CYP3A4 and to a lesser extent by flavin-containing monooxygenase (FMO).

Neratinib represents the most prominent component in plasma. The systemic exposures (AUC) of the active metabolites M3, M6, M7 and M11 were 15%, 33%, 22%, and 4% of the systemic neratinib exposure, respectively, at steady state in healthy subjects.

Excretion

After oral administration of radiolabeled neratinib 200 mg (0.83 times of maximum approved recommended dosage), fecal excretion accounted for approximately 97% and urinary excretion accounted for 1.1% of the total dose. Sixty-one percent of the excreted radioactivity was recovered within 96 hours and 98% was recovered after 10 days.

Specific Populations

Age, sex, race, and renal function do not have a clinically significant effect on neratinib pharmacokinetics.

Patients With Hepatic Impairment

Neratinib exposures in patients with mild (Child Pugh A) and moderate hepatic impairment (Child Pugh B) were similar to that in healthy subjects with normal hepatic function. Neratinib Cmaxand AUC increased by 173% and 181%, respectively, in patients with severe hepatic impairment (Child Pugh C) as compared to subjects with normal hepatic function [see Dosage and Administration (2.4) and Use in Specific Populations (8.6)] .

Drug Interaction Studies

Clinical Studies and Model-Informed Approaches

Gastric Acid Reducing Agents:Concomitant use with lansoprazole (proton pump inhibitor) decreased neratinib Cmaxby 71% and AUC by 65%. When NERLYNX was administered 2 hours after ranitidine (H2receptor antagonist), the neratinib Cmaxwas reduced by 57% and AUC by 48%. When NERLYNX was administered 2 hours prior to ranitidine, neratinib Cmaxwas reduced by 44% and AUC by 32% [see Dosage and Administration (2.5) and Drug Interactions (7.1)] .

Strong CYP3A4 Inhibitors:Concomitant use of ketoconazole (strong inhibitor of CYP3A4 and P-gp inhibitor) increased neratinib Cmaxby 221% and AUC by 381% [see Drug Interactions (7.1)] .

P-gp and moderate CYP3A4 Dual Inhibitors:Verapamil (moderate CYP3A4 and P-gp dual inhibitor) increased the Cmaxand AUC of neratinib by 203% and 299%, respectively [see Drug Interactions (7.1)] .

Moderate CYP3A4 Inhibitors:Fluconazole (moderate CYP3A4 inhibitor) increased the Cmaxand AUC of neratinib by 30% and 68%, respectively.

Strong and Moderate CYP3A4 Inducers:Concomitant use of rifampin (strong CYP3A4 inducer) decreased neratinib Cmaxby 76% and AUC by 87%. The AUC of active metabolites M6 and M7 were also reduced by 37–49% when compared to NERLYNX administered alone. Efavirenz (moderate CYP3A4 inducer) decreased the Cmaxof neratinib by 36% and AUC by 52% [see Drug Interactions (7.1)] .

Effect of NERLYNX on P-gp Transporters:Concomitant use of NERLYNX increased the mean digoxin (P-gp substrate) Cmaxby 54% and AUC by 32% [see Drug Interactions (7.2)] .

13 NONCLINICAL TOXICOLOGY

13.1 Carcinogenesis, Mutagenesis, Impairment of Fertility

A two-year carcinogenicity study was conducted in rats at oral neratinib doses of 1, 3, and 10 mg/kg/day. Neratinib was not carcinogenic in male and female rats at exposure levels >25 times the AUC in patients receiving the maximum recommended dose of 240 mg/day. Neratinib was not carcinogenic in a 26-week study in Tg.rasH2 transgenic mice when administered daily by oral gavage at doses up to 50 mg/kg/day in males and 125 mg/kg/day in females.

Neratinib was not mutagenic in an in vitrobacterial reverse mutation (AMES) assay or clastogenic in an in vitrohuman lymphocyte chromosomal aberration assay or an in vivorat bone marrow micronucleus assay.

In a fertility study in rats, neratinib administration up to 12 mg/kg/day (approximately 0.5 times the maximum recommended dose of 240 mg/day in patients on a mg/m^2basis) caused no effects on mating or the ability of animals to become pregnant. In repeat-dose toxicity studies in dogs with oral administration of neratinib daily for up to 39 weeks, tubular hypoplasia of the testes was observed at ≥0.5 mg/kg/day. This finding was observed at AUCs that were approximately 0.4 times the AUC in patients at the maximum recommended dose of 240 mg.

14 CLINICAL STUDIES

14.1 Extended Adjuvant Treatment of Early-Stage Breast Cancer

The safety and efficacy of NERLYNX were investigated in the ExteNET trial (NCT00878709), a multicenter, randomized, double-blind, placebo-controlled study of NERLYNX after adjuvant treatment with a trastuzumab based therapy in women with HER2-positive breast cancer.

A total of 2840 patients with early-stage (Stage 1 to 3c) HER2-positive breast cancer within two years of completing treatment with adjuvant trastuzumab was randomized to receive either NERLYNX (n=1420) or placebo (n=1420). Randomization was stratified by the following factors: hormone receptor status, nodal status (0, 1–3, vs 4 or more positive nodes) and whether trastuzumab was given sequentially versus concurrently with chemotherapy. NERLYNX 240 mg or placebo was given orally once daily for one year. The major efficacy outcome measure was invasive disease-free survival (iDFS) defined as the time between the date of randomization to the first occurrence of invasive recurrence (local/regional, ipsilateral, or contralateral breast cancer), distant recurrence, or death from any cause, with 2 years and 28 days of follow-up.

Patient demographics and tumor characteristics were generally balanced between treatment arms. Patients had a median age of 52 years (range 23 to 83) and 12% of patients were 65 or older. The majority of patients were White (81%), and most patients (99.7%) had an ECOG performance status of 0 or 1. Fifty-seven percent (57%) of patients had hormone receptor positive disease (defined as ER-positive and/or PR-positive), 24% were node negative, 47% had one to three positive nodes and 30% had four or more positive nodes. Ten percent (10%) of patients had Stage I disease, 41% had Stage II disease and 31% had Stage III disease. The majority of patients (81%) were enrolled within one year of completion of trastuzumab treatment. Median time from the last adjuvant trastuzumab treatment to randomization was 4.4 months in the NERLYNX arm versus 4.6 months in the placebo arm. Median duration of treatment was 11.6 months in the NERLYNX arm vs 11.8 months in the placebo arm.

The efficacy results from the ExteNET trial are summarized in Table 11and Figure 1.

Table 11: Efficacy iDFS Results for the ITT Population
Number of Events/Total N (%) |  | iDFS at 24 months,* % (95% CI) |  | Stratified†HR (95% CI) | P-value‡
NERLYNX | Placebo | NERLYNX | Placebo | Stratified†HR (95% CI) | P-value‡
67/1420 (4.7) | 106/1420 (7.5) | 94.2 (92.6, 95.4) | 91.9 (90.2, 93.2) | 0.66 (0.49, 0.90) | 0.008
CI= Confidence Interval; HR=Hazard Ratio; iDFS=Invasive Disease Free-Survival; ITT=Intent to Treat
* Kaplan-Meier estimate
† Stratified by prior trastuzumab (concurrent vs sequential), nodal status (0–3 positive nodes vs ≥4 positive nodes), and ER/PR status (positive vs negative)
‡ Stratified log-rank test

Figure 1: iDFS in the ExteNET Trial - ITT Population

CI=Confidence Interval; iDFS=Invasive Disease Free-Survival; ITT=Intent to Treat

Table 12: Subgroup Analyses*
Population | Number of Events/Total N (%) |  | iDFS at 24 Months,†% (95% CI) |  | Unstratified HR (95% CI)
Population | NERLYNX | Placebo | NERLYNX | Placebo | Unstratified HR (95% CI)
Hormone Receptor Status
Positive | 29/816 (3.6) | 63/815 (7.7) | 95.6 (93.8, 96.9) | 91.5 (89.2, 93.3) | 0.49 (0.31, 0.75)
Negative | 38/604 (6.3) | 43/605 (7.1) | 92.2 (89.4, 94.3) | 92.4 (89.8, 94.3) | 0.93 (0.60, 1.43)
Nodal Status
Negative | 7/335 (2.1) | 11/336 (3.3) | 97.2 (94.1, 98.7) | 96.5 (93.7, 98.0) | 0.72 (0.26, 1.83)
1–3 Positive Nodes | 31/664 (4.7) | 47/664 (7.1) | 94.4 (92.2, 96.1) | 92.4 (90.0, 94.2) | 0.68 (0.43, 1.07)
≥4 Positive Nodes | 29/421 (6.9) | 48/420 (11.4) | 91.4 (87.9, 94.0) | 87.3 (83.4, 90.2) | 0.62 (0.39, 0.97)
Prior Trastuzumab
Concurrent | 49/884 (5.5) | 66/886 (7.4) | 93.2 (91.0, 94.8) | 92.0 (89.9, 93.7) | 0.80 (0.55, 1.16)
Sequential | 18/536 (3.4) | 40/534 (7.5) | 95.8 (93.4, 97.3) | 91.6 (88.7, 93.8) | 0.46 (0.26, 0.78)
Completion of Prior Trastuzumab
≤1 Year | 58/1152 (5.0) | 95/1145 (8.3) | 93.8 (92.0, 95.2) | 90.9 (89.0, 92.5) | 0.63 (0.45, 0.88)
1–2 Years | 9/262 (3.4) | 11/270 (4.1) | 95.8 (92.0, 97.8) | 95.7 (92.3, 97.6) | 0.92 (0.37, 2.22)
CI=Confidence Interval; HR=Hazard Ratio
* Exploratory analyses without adjusting multiple comparisons
† Kaplan-Meier estimate

Approximately 75% of patients were re-consented for extended follow-up beyond 24 months. Observations with missing data were censored at the last date of assessment. This exploratory analysis suggests that the iDFS results at 5 years are consistent with the 2-year iDFS results observed in ExteNET. After a median follow-up of 8 years, there was no statistically significant difference in OS between the NERLYNX arm and the placebo arm [HR 0.95 (95% CI: 0.75, 1.21)]. The 5-year estimate of OS was 94.1% (95% CI, 92.7%, 95.3%) in the NERLYNX arm and 93.3% (95% CI, 91.8%, 94.5%) in the placebo arm.

14.2 Advanced or Metastatic Breast Cancer

The safety and efficacy of NERLYNX in combination with capecitabine was studied in NALA (NCT01808573), a randomized, multicenter, open-label clinical trial in patients (n=621) with metastatic HER2 positive breast cancer who had received 2 or more prior anti-HER2 based regimens in the metastatic setting. HER2 expression was based on archival tissue tested at a central laboratory prior to enrollment. HER2 positivity was defined as a HER2 immunohistochemistry (IHC) score of 3+ or IHC 2+ with confirmatory in situ hybridization (ISH) positive. Fifty-nine percent of these patients were hormone receptor positive (HR+) and 41% were hormone receptor negative (HR-); 69% had received two prior anti-HER2 based regimens, 31% had received three or more prior anti-HER2 based regimens, 81% had visceral disease, and 19% had non-visceral-only disease. Patients with asymptomatic or stable brain metastases were included in NALA trial (16%).

Patients were randomized (1:1) to receive NERLYNX 240 mg orally once daily on Days 1–21 in combination with capecitabine 750 mg/m^2given orally twice daily on Days 1–14 for each 21-day cycle (n=307) or lapatinib 1250 mg orally once daily Days 1–21 in combination with capecitabine 1000 mg/m^2given orally twice daily on Days 1–14 for each 21-day cycle (n=314). Patients were treated until disease progression or unacceptable toxicity.

The efficacy results from the NALA trial are summarized in Table 13, Figure 2, and Figure 3.

Table 13. Efficacy Results – NALA Trial (Central Assessment)
 | NERLYNX + Capecitabine (n=307) | Lapatinib + Capecitabine (n=314)
Progression-Free Survival (PFS)
Number of Events (%) | 210 (68.4) | 223 (71.0)
Median PFS, months (95% CI) | 5.6 (4.9, 6.9) | 5.5 (4.3, 5.6)
HR (95% CI)* | 0.76 (0.63,0.93)
p-value† | 0.0059
PFS Rates at 12 Months, % (95% CI) | 29 (23, 35) | 15 (10, 20)
PFS Rates at 24 Months, % (95% CI)‡ | 12 (7, 18) | 3 (1, 8)
Overall Survival (OS)
Number of Events (%) | 192 (62.5) | 218 (69.4)
Median OS, months (95% CI) | 21.0 (17.7, 23.8) | 18.7 (15.5, 21.2)
HR (95% CI)* | 0.88 (0.72, 1.07)
p-value† | 0.2086
Objective Response Rate (ORR)§
ORR, % (95% CI) | 32.8 (27.1, 38.9) | 26.7 (21.5, 32.4)
Duration of Response (DOR)
Median DOR, months (95% CI) | 8.5 (5.6, 11.2) | 5.6 (4.2, 6.4)
HR=Hazard Ratio
* Hazard ratio is presented as NERLYNX plus Capecitabine (N+C) vs Lapatinib plus Capecitabine (L+C).
† Stratified log-rank test
‡ The total number of patients remaining on study at 24 months is 11; with 9 patients on N+C and 2 patients on L+C.
§ Confirmed ORR in patients with measurable disease at screening (256 in the N+C arm and 270 in the L+C arm)

Figure 2. Progression-Free Survival (Central Assessment - ITT Population)

CI=Confidence Interval; ITT=Intent to Treat; L+C=Lapatinib plus Capecitabine; N+C=NERLYNX plus Capecitabine

Figure 3. Overall Survival (ITT Population)

ITT=Intent to Treat; L+C=Lapatinib plus Capecitabine; N+C=NERLYNX plus Capecitabine

Table 14. Progression-Free Survival Rates - Subgroup Analysesα
Population | Number of Events/Total N (%) |  | PFS Rates (%) at 12 Months (95% CI)
Population | NERLYNX + Capecitabine | Lapatinib + Capecitabine | NERLYNX + Capecitabine | Lapatinib + Capecitabine
Disease Location
Visceral | 181/247 (73.3) | 185/253 (73.1) | 23 (17, 30) | 14 (10, 20)
Non-Visceral | 29/60 (48.3) | 38/61 (62.3) | 53 (38, 66) | 18 (7, 32)
Hormone Receptor Status
Positive | 128/181 (70.7) | 115/186 (61.8) | 27 (19, 34) | 23 (15, 31)
Negative | 82/126 (65.1) | 108/128 (84.4) | 32 (23, 41) | 5 (2, 11)
Previous HER2 Regimens
2 Regimens | 148/215 (68.8) | 151/215 (70.2) | 26 (20, 33) | 13 (8, 19)
≥3 Regimens | 62/92 (67.4) | 72/99 (72.7) | 34 (24, 45) | 19 (11, 29)
CI=Confidence Interval; PFS=Progression-Free Survival
α Exploratory Analysis

16 HOW SUPPLIED/STORAGE AND HANDLING

NERLYNX 40 mg film-coated tablets are red, oval shaped and debossed with 'W104' on one side and plain on the other side.

NERLYNX is available in:

- Bottles of 180 tablets: NDC 70437-240-18
- Bottles of 133 tablets: NDC 70437-240-33
- Bottles of 126 tablets: NDC 70437-240-26

Store at controlled room temperature, 20°C to 25°C (68°F to 77°F); excursions permitted to 15°C to 30°C (59°F to 86°F) [see USP Controlled Room Temperature].

17 PATIENT COUNSELING INFORMATION

Advise the patient to read the FDA-approved patient labeling (Patient Information).

Diarrhea

- Inform patients that NERLYNX has been associated with diarrhea, which may be severe in some cases.
- When not using dose escalation, instruct patients to initiate antidiarrheal prophylaxis with the first dose of NERLYNX.
- When using dose escalation, instruct patients to initiate 2 weeks of lower dose NERLYNX prior to receiving the recommended full dose of NERLYNX.
- Instruct patients to maintain 1–2 bowel movements per day and on how to use antidiarrheal treatment regimens.
- Advise patients to inform their healthcare provider immediately if severe (≥Grade 3) diarrhea or diarrhea associated with weakness, dizziness, or fever occurs during treatment with NERLYNX [see Dosage and Administration (2.1, 2.2) and Warnings and Precautions (5.1)] .

Hepatotoxicity

- Inform patients that NERLYNX has been associated with hepatotoxicity which may be severe in some cases.
- Inform patients that they should report signs and symptoms of liver dysfunction to their healthcare provider immediately [see Warnings and Precautions (5.2)] .

Embryo-Fetal Toxicity

- Advise females to inform their healthcare provider if they are pregnant or become pregnant. Inform female patients of the risk to a fetus and potential loss of the pregnancy [see Use in Specific Populations (8.1)] .
- Advise females of reproductive potential to use effective contraception during treatment and for 1 month after receiving the last dose of NERLYNX [see Warnings and Precautions (5.3) and Use in Specific Populations (8.1, 8.3)] .
- Advise lactating women not to breastfeed during treatment with NERLYNX and for at least 1 month after the last dose [see Use in Specific Populations (8.2)] .

Drug Interactions

- NERLYNX may interact with many drugs; therefore, advise patients to report to their healthcare provider the use of any other prescription or nonprescription medication or herbal products [see Dosage and Administration (2.5) and Clinical Pharmacology (12.3)] .
- NERLYNX may interact with gastric acid reducing agents. Advise patients to avoid concomitant use of proton pump inhibitors. When patients require gastric acid reducing agents, use an H2-receptor antagonist or antacid. Advise patients to separate the dosing of NERLYNX by 3 hours after antacid medicine, and to take NERLYNX at least 2 hours before or 10 hours after a H2-receptor antagonist [see Dosage and Administration (2.5) and Drug Interactions (7.1)] .
- NERLYNX may interact with grapefruit. Advise patients to avoid taking NERLYNX with grapefruit products [see Drug Interactions (7.1)] .

Dosing and Administration

- For patients undergoing extended adjuvant treatment for early-stage breast cancer, instruct patients to take NERLYNX with food at approximately the same time each day consecutively until disease recurrence or for up to one year.
- For patients undergoing treatment for metastatic breast cancer, instruct patients to take NERLYNX with food on days 1–21 of a 21-day cycle, with capecitabine on Days 1–14 of a 21-day cycle until disease progression or unacceptable toxicities.
- If a patient misses a dose, instruct the patient not to replace the missed dose, and to resume NERLYNX with the next scheduled daily dose [see Dosage and Administration (2.2)] .

Manufactured for Puma Biotechnology, Inc.
10880 Wilshire Blvd., Suite 1700
Los Angeles, CA 90024-4106

©2025, Puma Biotechnology, Inc. All Rights Reserved.

PATIENT INFORMATION
NERLYNX® (ner links)
(neratinib)
tablets

What is the most important information I should know about NERLYNX?
NERLYNX may cause serious side effects, including:

- Diarrhea.Diarrhea is a common side effect of NERLYNX, but it can also be severe. Diarrhea may lead to loss of too much body salts and fluid, which can cause dehydration.
  Your healthcare provider will prescribe NERLYNX in one of two ways to help manage diarrhea:
  Full dose of NERLYNX:
  - Your healthcare provider will prescribe the antidiarrheal medicine loperamide for you during your first 2 months (56 days) of treatment with NERLYNX and then as needed. Your healthcare provider will tell you exactly how much and how often to take this medicine.
  - If you are prescribed the full dose of NERLYNX from the start of your treatment, be sure that your healthcare provider also prescribes antidiarrheals with NERLYNX. You should start taking loperamide with your first dose of NERLYNX.
  - After 2 months (56 days) of treatment with NERLYNX, follow your healthcare provider's instructions about taking loperamide as needed to control diarrhea.
  A lower starting dose of NERLYNX:
  - Your healthcare provider will start you on a lower dose of NERLYNX for the first 2 weeks of treatment and then increase you to a full dose NERLYNX regimen. Tell your healthcare provider right away if you develop diarrhea. You may be prescribed loperamide as needed.
  To help prevent or reduce diarrhea during treatment with NERLYNX:
  - Your healthcare provider may also need to give you additional antidiarrheals, fluids, and electrolytes to manage diarrhea when you start treatment with NERLYNX. Follow your healthcare provider's instructions on how to take antidiarrheal medicines.
  - Always take antidiarrheals exactly as your healthcare provider tells you.
  - While taking antidiarrheals, you and your healthcare provider should try to keep the number of bowel movements that you have at 1 or 2 bowel movements each day.
  - Tell your healthcare provider if you have more than 2 bowel movements in 1 day, or you have diarrhea that does not go away.
  - Call your healthcare provider right away if you have severe diarrhea or if you have diarrhea along with weakness, dizziness, or fever.

Your healthcare provider may change your dose of NERLYNX, temporarily stop, or completely stop NERLYNX if needed to manage your diarrhea.
See " What are the possible side effects of NERLYNX?" for more information about side effects.

What is NERLYNX?

- NERLYNX is a prescription medicine used alone to treat adults with early-stage human epidermal growth factor receptor 2 (HER2)-positive breast cancer andwho have previously been treated with trastuzumab-based therapy.
- NERLYNX is also used with a medicine called capecitabine to treat adults with HER2-positive breast cancer that has spread to other parts of the body (metastatic) andwho have received 2 or more anti-HER2 therapy medicines for metastatic breast cancer.

It is not known if NERLYNX is safe and effective in children.

Before taking NERLYNX, tell your healthcare provider about all of your medical conditions, including if you:

- have liver problems. You may need a lower dose of NERLYNX.
- are pregnant or plan to become pregnant. NERLYNX can harm your unborn baby. If you are a female who can become pregnant:
  - Your healthcare provider should do a pregnancy test before you start taking NERLYNX.
  - You should use effective birth control (contraception) during treatment and for at least 1 month after your last dose of NERLYNX.
  - Talk with your healthcare provider about forms of birth control that you can use during this time.
  - Tell your healthcare provider right away if you become pregnant during treatment with NERLYNX.
  - Males with female partners who can become pregnant should use effective birth control during treatment and for 3 months after the last dose of NERLYNX.
- are breastfeeding or plan to breastfeed. It is not known if NERLYNX passes into your breast milk. Do not breastfeed during treatment and for at least 1 month after your last dose of NERLYNX.

Tell your healthcare provider about all the medicines you take,including prescription and over-the-counter medicines, vitamins, and herbal supplements.
Especially tell your healthcare provider ifyou take medicines used to decrease stomach acid, called proton pump inhibitors or PPIs. You should avoid taking these medicines during treatment with NERLYNX.

How should I take NERLYNX?

- Take NERLYNX exactly as your healthcare provider tells you to take it.
- Your healthcare provider may change your dose of NERLYNX if needed.
- Take NERLYNX with food.
- Take NERLYNX at about the same time each day.
- Swallow NERLYNX tablets whole. Do not chew, crush, or split NERLYNX tablets.
- If you take an antacid medicine, take NERLYNX 3 hours after the antacid medicine.
- If you take an acid reducer (H2receptor blocker), NERLYNX should be taken at least 2 hours before or 10 hours after you take these medicines.
- If you miss a dose of NERLYNX, skip that dose and take your next dose at your regular scheduled time.
- If you take too much NERLYNX, call your healthcare provider right away or go to the nearest hospital emergency room.

What should I avoid while taking NERLYNX?
You should avoid eating products that contain grapefruit during treatment with NERLYNX.

What are the possible side effects of NERLYNX?

NERLYNX may cause serious side effects, including:
See " What is the most important information I should know about NERLYNX?"

- Liver problems. Changes in liver function tests are common with NERLYNX. Your healthcare provider should do blood tests before you begin treatment, monthly during the first 3 months, and then every 3 months as needed during treatment with NERLYNX. Your healthcare provider will stop your treatment with NERLYNX if your liver tests show severe problems. Call your healthcare provider right away if you get any of the following signs or symptoms of liver problems:

- tiredness
- nausea
- vomiting
- pain in the right upper stomach-area (abdomen)

- fever
- rash
- itching
- yellowing of your skin or whites of your eyes

The most common side effectsof NERLYNX when used alone include:

- diarrhea
- nausea
- stomach-area (abdomen) pain
- tiredness
- vomiting
- rash
- dry or inflamed mouth, or mouth sores
- decreased appetite

- muscle spasms
- upset stomach
- nail problems including color change
- dry skin
- swelling of your stomach-area
- nosebleed
- weight loss
- urinary tract infection

The most common side effectsof NERLYNX when used with capecitabine include:

- diarrhea
- nausea
- vomiting
- decreased appetite
- constipation
- tiredness/weakness
- weight loss
- dizziness

- back pain
- joint pain
- urinary tract infection
- upper respiratory tract infection
- swelling of your stomach-area
- kidney problems
- muscle spasms

These are not all of the possible side effects of NERLYNX. For more information, ask your healthcare provider.
Tell your healthcare provider if you have any side effects that bother you or that does not go away.
Call your doctor for medical advice about side effects. You may report side effects to FDA at 1-800-FDA-1088.

How should I store NERLYNX?

- Store NERLYNX at room temperature between 68°F to 77°F (20°C to 25°C).

Keep NERLYNX and all medicines out of the reach of children.

General information about the safe and effective use of NERLYNX.
Medicines are sometimes prescribed for purposes other than those listed in a Patient Information leaflet. Do not use NERLYNX for a condition for which it was not prescribed. Do not give NERLYNX to other people, even if they have the same symptoms that you have. It may harm them. You can ask your pharmacist or healthcare provider for information about NERLYNX that is written for health professionals.

What are the ingredients in NERLYNX?
Active ingredient:neratinib
Inactive ingredients:Tablet Core: colloidal silicon dioxide, mannitol, microcrystalline cellulose, crospovidone, povidone, magnesium stearate, and purified water. Coating: red film coat: polyvinyl alcohol, titanium dioxide, polyethylene glycol, talc, and iron oxide red.
Manufactured for: Puma Biotechnology, Inc. 10880 Wilshire Blvd., Suite 1700 Los Angeles, CA 90024-4106
©2025, Puma Biotechnology, Inc. All rights reserved.
For more information, go to www.NERLYNX.com or call 1-844-637-5969.

This Patient Information has been approved by the U.S. Food and Drug Administration.

Revised: 12/2025

Principal Display Panel - Nerlynx 180 Tablets Carton Label

NDC 70437-240-18

nerlynx™
(neratinib) tablets

40 mg

Each film-coated tablet contains 40 mg neratinib
equivalent to 48.31 mg neratinib maleate.

180 tablets Rx only

Principal Display Panel - Nerlynx 180 Tablets Bottle Label

NDC 70437-240-18

nerlynx™
(neratinib) tablets

40 mg

Rx only 180 tablets

Principal Display Panel - Nerlynx 126 Tablets Carton Label

NDC 70437-240-26

nerlynx™
(neratinib) tablets

40 mg

Each film-coated tablet contains 40 mg neratinib
equivalent to 48.31 mg neratinib maleate.

126 tablets Rx only

Principal Display Panel - Nerlynx 126 Tablets Bottle Label

NDC 70437-240-26

nerlynx™
(neratinib) tablets

40 mg

Rx only 126 tablets

Principal Display Panel - Nerlynx 133 Tablets Carton Label

NDC 70437-240-33

nerlynx™
(neratinib) tablets

40 mg

Each film-coated tablet contains 40 mg neratinib
equivalent to 48.31 mg neratinib maleate.

133 tablets Rx only

Principal Display Panel - Nerlynx 133 Tablets Bottle Label

NDC 70437-240-33

nerlynx™
(neratinib) tablets

40 mg

Rx only 133 tablets